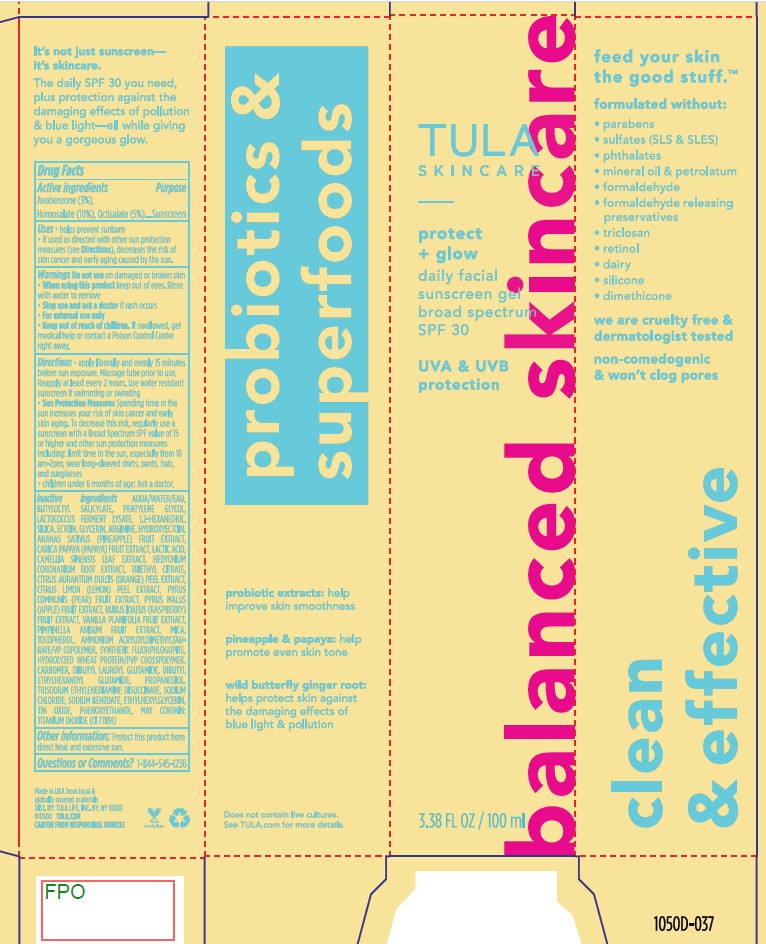 DRUG LABEL: Tula Skincare Protect and Glow Daily Facial Sunscreen Gel SPF 30
NDC: 84126-103 | Form: GEL
Manufacturer: The Procter & Gamble Manufacturing Company
Category: otc | Type: HUMAN OTC DRUG LABEL
Date: 20250318

ACTIVE INGREDIENTS: AVOBENZONE 3 g/100 mL; HOMOSALATE 10 g/100 mL; OCTISALATE 5 g/100 mL
INACTIVE INGREDIENTS: SODIUM BENZOATE; TITANIUM DIOXIDE; PHENOXYETHANOL; ANANAS SATIVUS (PINEAPPLE) FRUIT; PROPANEDIOL; LACTIC ACID; SILICA; ORANGE PEEL; DIBUTYL LAUROYL GLUTAMIDE; GLYCERIN; SODIUM CHLORIDE; MAGNESIUM POTASSIUM ALUMINOSILICATE FLUORIDE; TRIETHYL CITRATE; AMMONIUM ACRYLOYLDIMETHYLTAURATE/VP COPOLYMER; CITRUS LIMON (LEMON) PEEL; HYDROXYECTOIN; TRISODIUM ETHYLENEDIAMINE DISUCCINATE; CARBOMER; CAMELLIA SINENSIS LEAF; ECTOIN; PENTYLENE GLYCOL; MICA; BUTYLOCTYL SALICYLATE; ANISE; TOCOPHEROL; CARICA PAPAYA (PAPAYA) FRUIT; RUBUS IDAEUS (RASPBERRY) FRUIT; 1,2-HEXANEDIOL; ARGININE; HEDYCHIUM CORONARIUM ROOT; PYRUS MALUS (APPLE) FRUIT; WATER; DIBUTYL ETHYLHEXANOYL GLUTAMIDE; TIN OXIDE; VANILLA PLANIFOLIA FRUIT; ETHYLHEXYLGLYCERIN; PYRUS COMMUNIS (PEAR) FRUIT

Tula Skincare Protect and Glow Daily Facial Sunscreen Gel SPF 30

Drug Facts

ACTIVE INGREDIENT

Avobenzone 3.0%

Homosalate 10.0%

Octisalate 5.0%

PURPOSE

Sunscreen

Uses

- helps prevent sunburn
- if used as directed with other sun protection measures (see Directions), decreases the risk of skin cancer and early skin aging caused by the sun

Warnings

For external use only

Do not use on damaged or broken skin

When using this product keep out of eyes. Rinse with water to remove.

Stop use and ask a doctor if rash occurs

Keep out of reach of children. If product is swallowed, get medical help or contact a Poison Control Center right away.

Directions

- apply liberally 15 minutes before sun exposure
- reapply at least every 2 hours
- use water resistant sunscreen if swimming or sweating
- Sun Protection Measures. Spending time in the sun increases your risk of skin cancer and early skin aging. To decrease this risk, regularly use a sunscreen with a Broad Spectrum SPF value of 15 or higher and other sun protection measures including:
  - limit time in sun, especially from 10 a.m. – 2 p.m.
  - wear long-sleeved shirts, pants, hats, and sunglasses
- children under 6 months: ask a doctor

Other information

- protect this product from excessive heat and direct sun

Inactive ingredients

Water, Butyloctyl Salicylate, Pentylene Glycol, Lactococcus Ferment Lysate, 1,2-Hexanediol, Silica, Ectoin, Glycerin, Arginine, Hydroxyectoin, Ananas Sativus (Pineapple) Fruit Extract, Carica Papaya (Papaya) Fruit Extract, Lactic Acid, Camellia Sinensis Leaf Extract, Hedychium Coronarium Root Extract, Triethyl Citrate, Citrus Aurantium Dulcis (Orange) Peel Extract, Citrus Limon (Lemon) Peel Extract, Pyrus Communis (Pear) Fruit Extract, Pyrus Malus (Apple) Fruit Extract, Rubus Idaeus (Raspberry) Fruit Extract, Vanilla Planifolia Fruit Extract, Pimpinella Anisum Fruit Extract, Mica, Tocopherol, Ammonium Acryloyldimethyltaurate/VP Copolymer, Synthetic Fluorphlogopite, Hydrolyzed Wheat Protein/PVP Crosspolymer, Carbomer, Dibutyl Lauroyl Glutamide, Dibutyl Ethylhexanoyl Glutamide, Propanediol, Trisodium Ethylenediamine Disuccinate, Sodium Chloride, Sodium Benzoate, Ethylhexylglycerin, Tin Oxide, Phenoxyethanol
May Contain: Titanium Dioxide (CI 77891)

Questions or comments?

Call 1-844-545-1236

Dist. by TULA LIFE, INC.

NY, NY 10003

PACKAGE LABEL

TULA

SKINCARE

protect + glow

dailyi facial

sunscreen gel

BROAD SPECTRUM SPF 30

3.38 FL OZ (100 mL)